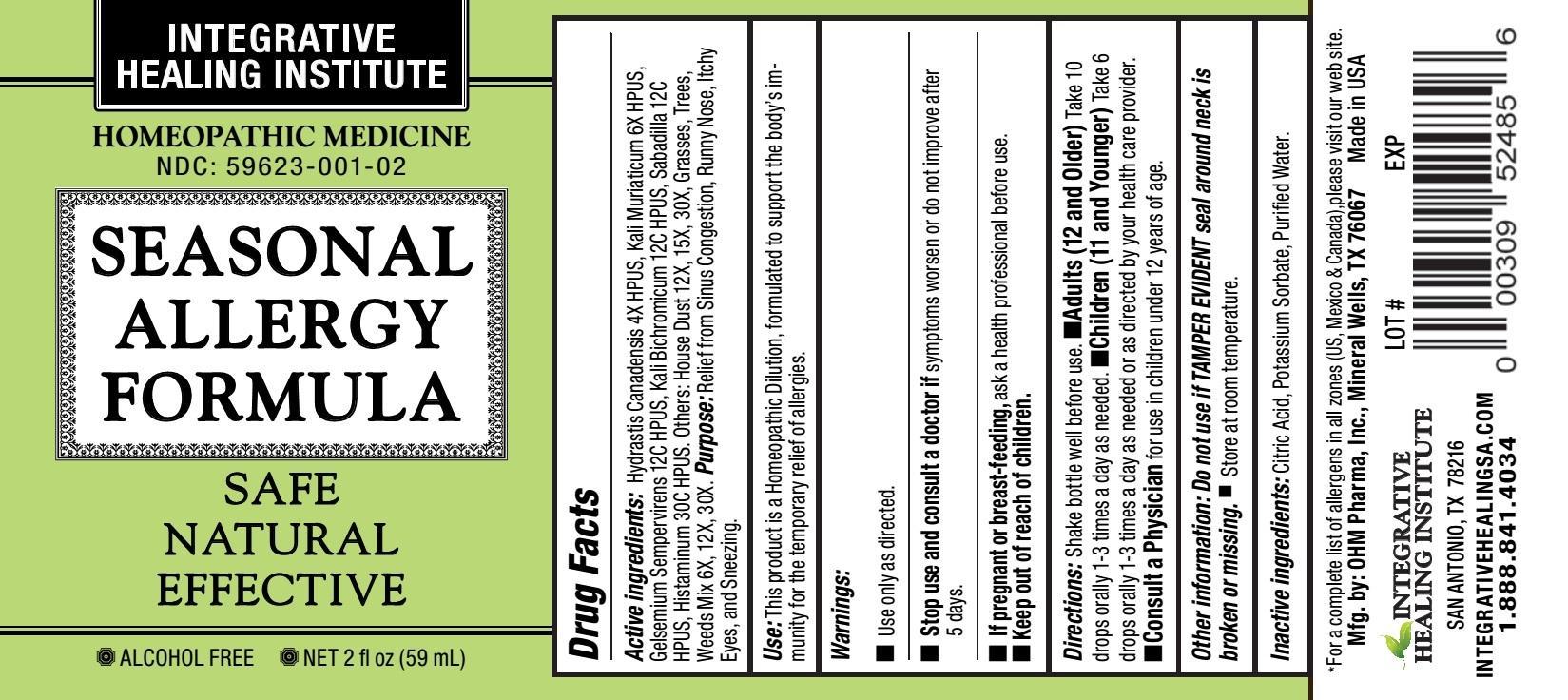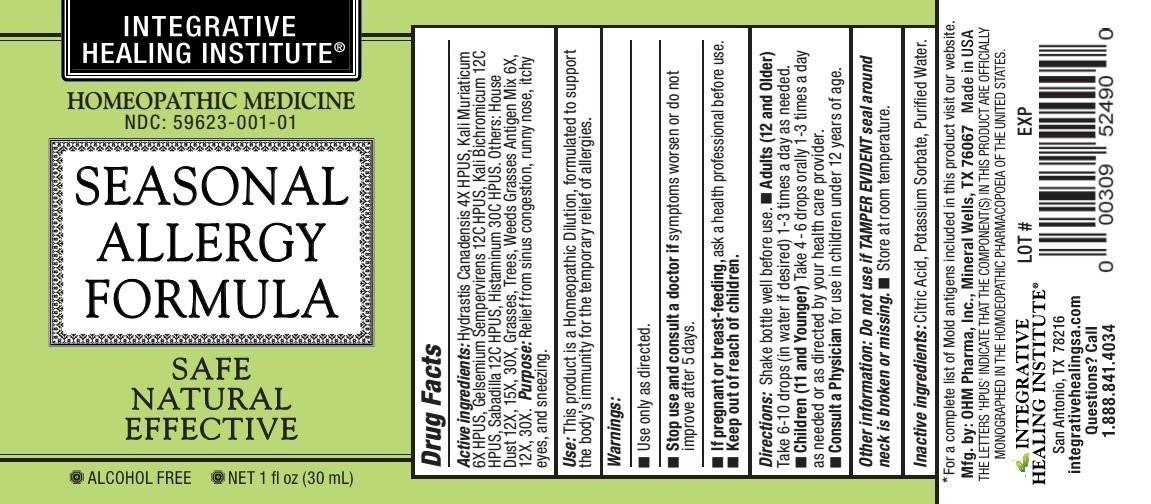 DRUG LABEL: Seasonal Allergy Formula
NDC: 59623-001 | Form: LIQUID
Manufacturer: Integrative Healing Institute, LLC
Category: homeopathic | Type: HUMAN OTC DRUG LABEL
Date: 20251017

ACTIVE INGREDIENTS: GOLDENSEAL 4 [hp_X]/1 mL; POTASSIUM CHLORIDE 6 [hp_X]/1 mL; GELSEMIUM SEMPERVIRENS ROOT 12 [hp_C]/1 mL; POTASSIUM DICHROMATE 12 [hp_C]/1 mL; SCHOENOCAULON OFFICINALE SEED 12 [hp_C]/1 mL; HISTAMINE DIHYDROCHLORIDE 30 [hp_C]/1 mL; HOUSE DUST 12 [hp_X]/1 mL; ANTHOXANTHUM ODORATUM 6 [hp_X]/1 mL; BROMUS SECALINUS POLLEN 6 [hp_X]/1 mL; CYNODON DACTYLON POLLEN 6 [hp_X]/1 mL; BARLEY 6 [hp_X]/1 mL; SORGHUM HALEPENSE POLLEN 6 [hp_X]/1 mL; POA PRATENSIS POLLEN 6 [hp_X]/1 mL; MELILOTUS OFFICINALIS TOP 6 [hp_X]/1 mL; PHLEUM PRATENSE TOP 6 [hp_X]/1 mL; TRITICUM AESTIVUM POLLEN 6 [hp_X]/1 mL; ZEA MAYS POLLEN 6 [hp_X]/1 mL; AMARANTHUS RETROFLEXUS POLLEN 6 [hp_X]/1 mL; AMBROSIA ARTEMISIIFOLIA POLLEN 6 [hp_X]/1 mL; RUMEX ACETOSELLA POLLEN 6 [hp_X]/1 mL; SOLIDAGO VIRGAUREA POLLEN 6 [hp_X]/1 mL; ARTEMISIA VULGARIS POLLEN 6 [hp_X]/1 mL; ALNUS RUBRA POLLEN 6 [hp_X]/1 mL; FRAXINUS PENNSYLVANICA POLLEN 6 [hp_X]/1 mL; FRAXINUS AMERICANA POLLEN 6 [hp_X]/1 mL; BETULA PAPYRIFERA POLLEN 6 [hp_X]/1 mL; BETULA NIGRA POLLEN 6 [hp_X]/1 mL; BETULA LENTA POLLEN 6 [hp_X]/1 mL; BETULA PUBESCENS FLOWER BUD 6 [hp_X]/1 mL; ACER NEGUNDO POLLEN 6 [hp_X]/1 mL; ULMUS AMERICANA POLLEN 6 [hp_X]/1 mL; ULMUS PUMILA POLLEN 6 [hp_X]/1 mL; ULMUS RUBRA POLLEN 6 [hp_X]/1 mL; CARYA GLABRA POLLEN 6 [hp_X]/1 mL; CARYA OVATA POLLEN 6 [hp_X]/1 mL; CARYA LACINIOSA POLLEN 6 [hp_X]/1 mL; CARYA TOMENTOSA POLLEN 6 [hp_X]/1 mL; ACER RUBRUM POLLEN 6 [hp_X]/1 mL; ACER SACCHARINUM POLLEN 6 [hp_X]/1 mL; ACER SACCHARUM POLLEN 6 [hp_X]/1 mL; QUERCUS MARILANDICA POLLEN 6 [hp_X]/1 mL; QUERCUS MACROCARPA POLLEN 6 [hp_X]/1 mL; QUERCUS STELLATA POLLEN 6 [hp_X]/1 mL; QUERCUS RUBRA POLLEN 6 [hp_X]/1 mL; QUERCUS ALBA POLLEN 6 [hp_X]/1 mL; PINUS NIGRA POLLEN 6 [hp_X]/1 mL; PINUS TAEDA POLLEN 6 [hp_X]/1 mL; PINUS SYLVESTRIS POLLEN 6 [hp_X]/1 mL; PINUS STROBUS POLLEN 6 [hp_X]/1 mL; MORUS RUBRA POLLEN 6 [hp_X]/1 mL; JUNIPERUS VIRGINIANA POLLEN 6 [hp_X]/1 mL; PLATANUS OCCIDENTALIS POLLEN 6 [hp_X]/1 mL; JUGLANS REGIA POLLEN 6 [hp_X]/1 mL; POPULUS ALBA POLLEN 6 [hp_X]/1 mL; PLANTAGO LANCEOLATA POLLEN 6 [hp_X]/1 mL
INACTIVE INGREDIENTS: CITRIC ACID MONOHYDRATE; POTASSIUM SORBATE; WATER

SEASONAL ALLERGY FORMULA

ACTIVE INGREDIENT

Active ingredients:Hydrastis Canadensis 4X HPUS, Kali Muriaticum 6X HPUS, Gelsemium Sempervirens 12C HPUS, Kali Bichromicum 12C HPUS, Sabadilla 12C HPUS, Histaminum 30C HPUS. Others: House Dust 12X, 15X, 30X, Grasses, Trees, Weeds Antigen Mix 6X, 12X, 30X.

PURPOSE

Purpose:Relief from sinus congestion, runny nose, itchy eyes, and sneezing.

INDICATIONS AND USAGE

Use:This product is a Homeopathic Dilution, formulated to support the body's immunity for the temporary relief of allergies.

Warnings:

- Use only as directed.
- Stop use and consult a doctor ifsymptoms worsen or do not improve after 5 days.
- If pregnant or breast-feeding,ask a health professional before use.

- Keep out of reach of children.

DOSAGE AND ADMINISTRATION

Directions:Shake bottle well before use.

- Adults (12 and Older)Take 6-10 drops orally (in water if desired) 1-3 times a day as needed.
- Children (11 and Younger)Take 4 - 6 drops orally 1-3 times a day as needed or as directed by your health care provider.
- Consult a Physicianfor use in children under 12 years of age.

Other information: Do not use if TAMPER EVIDENT seal around neck is broken or missing.

- Store at room temperature.

Inactive ingredients:Citric Acid, Potassium Sorbate, Purified Water.

OTHER SAFETY INFORMATION

*For a complete list of allergens in all zones (US, Mexico and Canada), please visit our web site.

*For a complete list of Mold antigens included in this product visit our website.

Mfg. by: OHM Pharma, Inc., Mineral Wells, TX 76067

Made in USA

THE LETTERS 'HPUS' INDICATE THAT THE COMPONENTS IN THIS PRODUCT ARE OFFICIALLY MONOGRAPHED IN THE HOMOEOPATHIC PHARMACOPOEIA OF THE UNITED STATES.

QUESTIONS

INTEGRATIVE HEALING INSTITUTE®

San Antonio, TX 78216

integrativehealingsa.com

Questions? Call

1.888.841.4034

PACKAGE LABEL

INTEGRATIVE HEALING INSTITUTE®

HOMEOPATHIC MEDICINE

- NDC: 59623-001-01
- NDC: 59623-001-02

SEASONAL ALLERGY FORMULA

- SAFE
- NATURAL
- EFFECTIVE

- ALCOHOL FREE

- NET 1 fl oz (30 mL)
- NET 2 fl oz (59 mL)